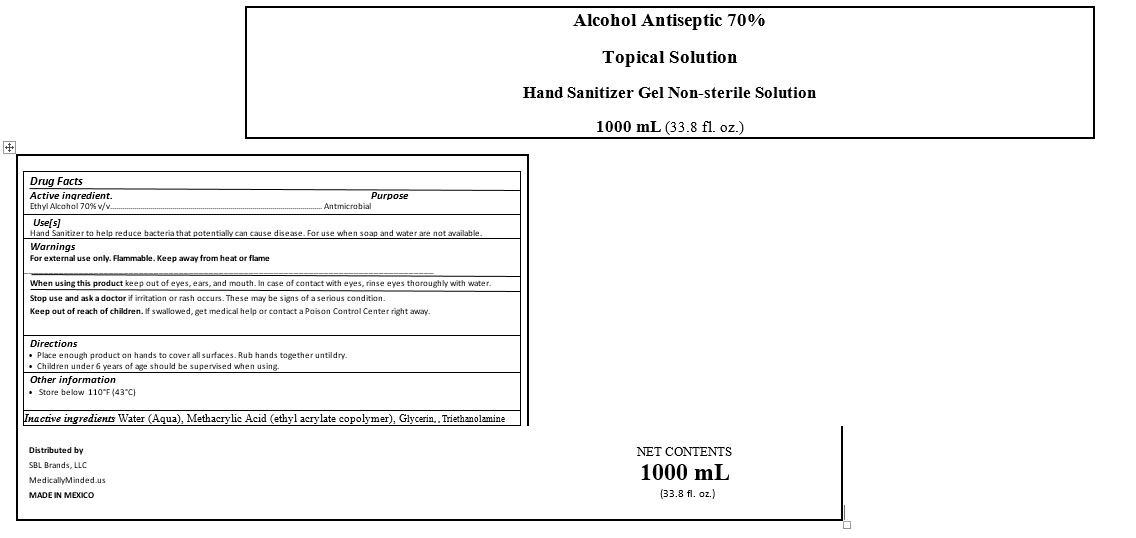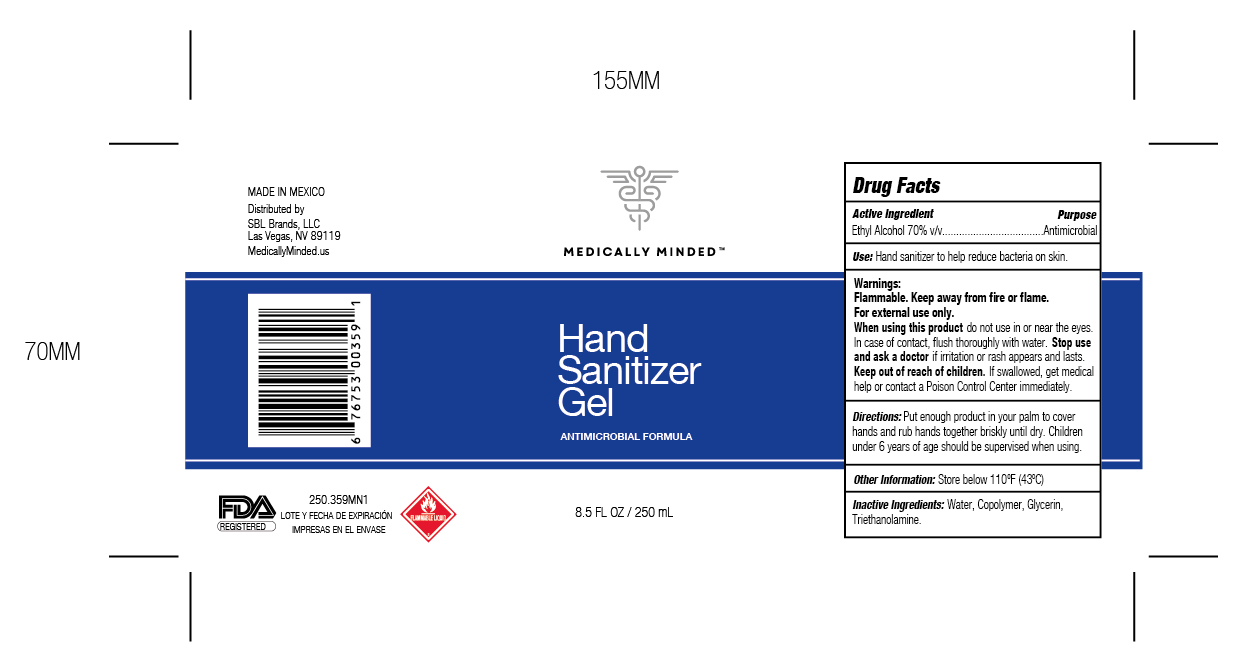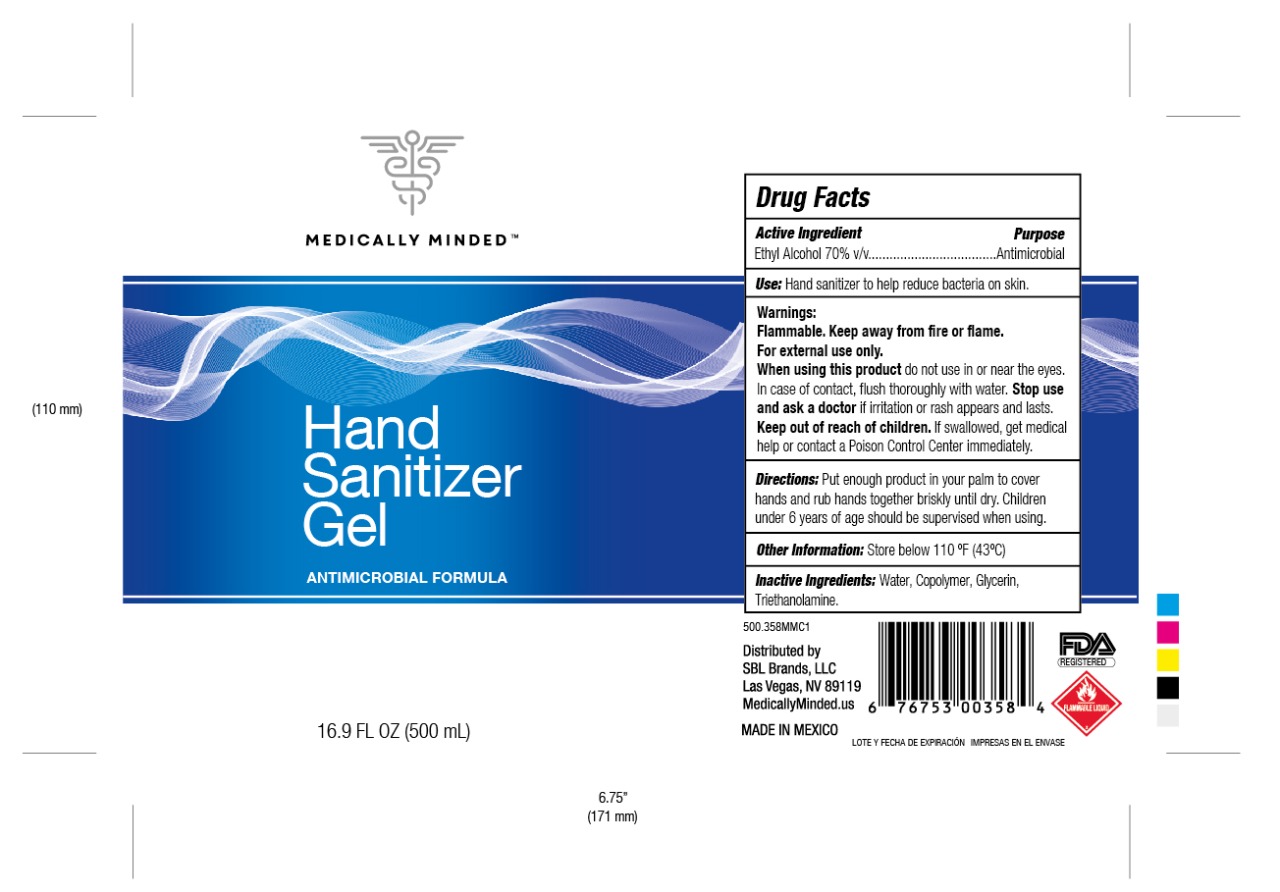 DRUG LABEL: HAND SANITIZER
NDC: 78814-6000 | Form: GEL
Manufacturer: FARMIRAL, S.A. DE C.V.
Category: otc | Type: HUMAN OTC DRUG LABEL
Date: 20200610

ACTIVE INGREDIENTS: ALCOHOL 0.7 mL/1 mL
INACTIVE INGREDIENTS: GLYCERIN 0.025 mL/1 mL; TROLAMINE 0.01 mL/1 mL; WATER 0.205 mL/1 mL; METHACRYLIC ACID - ETHYL ACRYLATE COPOLYMER (4500 MPA.S) 0.06 mL/1 mL

HAND SANITIZER GEL

DOSAGE AND ADMINISTRATION

Directions

Place enough product on hands to cover all surfaces. Rub hands together until dry.

INACTIVE INGREDIENTS

Inactive ingredients Water (Aqua), Glycerin, Carbomer, Triethanolamine

INDICATIONS

Directions

Place enough product on hands to cover all surfaces. Rub hands together until dry.

Keep out of reach of children. If swallowed, get medical help or contact a Poison Control Center right away.

ACTIVE INGREDIENT

Active ingredient. Ethyl Alcohol 70% v/v…

PURPOSE

Purpose Antmicrobial

WARNINGS AND PRECAUTIONS

Store below 110°F (43°C)

Children under 6 years of age should be supervised when using.

WARNING

Warnings

For external use only. Flammable. Keep away from heat or flame

STOP USE

Stop use and ask a doctor if irritation or rash occurs. These may be signs of a serious condition.